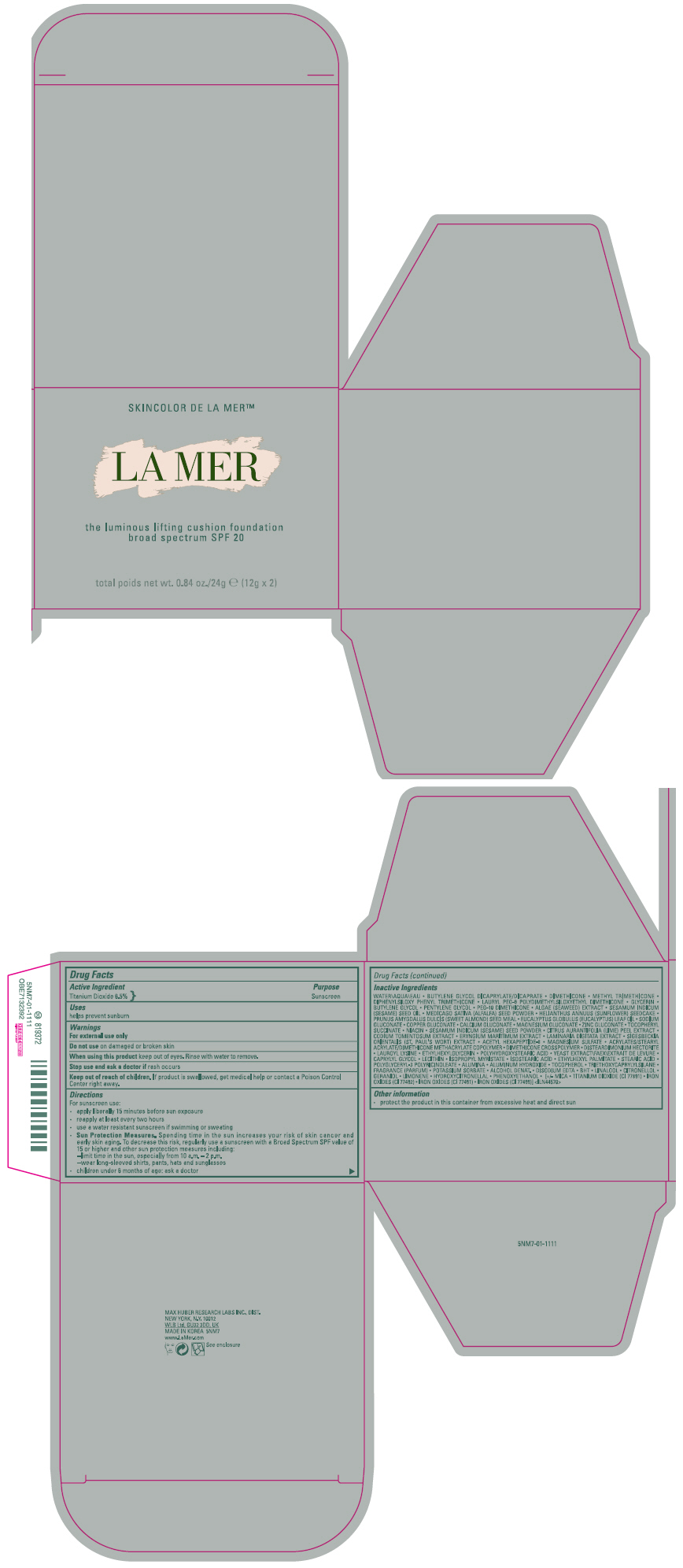 DRUG LABEL: LA MER THE LUMINOUS LIFTING CUSHION FOUNDATION BROAD SPECTRUM SPF 20
NDC: 65966-019 | Form: LOTION
Manufacturer: MAX HUBER RESEARCH LAB INC
Category: otc | Type: HUMAN OTC DRUG LABEL
Date: 20241225

ACTIVE INGREDIENTS: TITANIUM DIOXIDE 6.5 g/100 g
INACTIVE INGREDIENTS: CAPRYLYL GLYCOL; ISOPROPYL MYRISTATE; ISOSTEARIC ACID; ETHYLHEXYL PALMITATE; STEARIC ACID; ALUMINUM OXIDE; ALUMINUM HYDROXIDE; TOCOPHEROL; TRIETHOXYCAPRYLYLSILANE; POTASSIUM SORBATE; ALCOHOL; EDETATE DISODIUM ANHYDROUS; BUTYLATED HYDROXYTOLUENE; LINALOOL, (+/-)-; .BETA.-CITRONELLOL, (R)-; GERANIOL; LIMONENE, (+)-; HYDROXYCITRONELLAL; YEAST, UNSPECIFIED; PHENOXYETHANOL; MICA; FERRIC OXIDE YELLOW; FERRIC OXIDE RED; FERROSOFERRIC OXIDE; WATER; BUTYLENE GLYCOL DICAPRYLATE/DICAPRATE; DIMETHICONE; METHYL TRIMETHICONE; DIPHENYLSILOXY PHENYL TRIMETHICONE; LAURYL PEG-9 POLYDIMETHYLSILOXYETHYL DIMETHICONE; GLYCERIN; BUTYLENE GLYCOL; PENTYLENE GLYCOL; PEG-10 DIMETHICONE (600 CST); SESAME OIL; ALFALFA SEED; HELIANTHUS ANNUUS SEEDCAKE; EUCALYPTUS OIL; SODIUM GLUCONATE; COPPER GLUCONATE; CALCIUM GLUCONATE; MAGNESIUM GLUCONATE; ZINC GLUCONATE; .ALPHA.-TOCOPHEROL SUCCINATE, D-; NIACIN; LIME PEEL; CODIUM TOMENTOSUM; ERYNGIUM MARITIMUM WHOLE; LAMINARIA DIGITATA; ACETYL HEXAPEPTIDE-8; MAGNESIUM SULFATE, UNSPECIFIED FORM; DIMETHICONE CROSSPOLYMER (450000 MPA.S AT 12% IN CYCLOPENTASILOXANE); DISTEARDIMONIUM HECTORITE; LAUROYL LYSINE; ETHYLHEXYLGLYCERIN

LA MER THE LUMINOUS LIFTING CUSHION FOUNDATION BROAD SPECTRUM SPF 20

Drug Facts

Active Ingredient

Titanium Dioxide 6.5%

Purpose

Sunscreen

Uses

helps prevent sunburn

Warnings

For external use only

Do not use on damaged or broken skin

When using this product keep out of eyes. Rinse with water to remove.

Stop use and ask a doctor if rash occurs

Keep out of reach of children. If product is swallowed, get medical help or contact a Poison Control Center right away.

Directions

For sunscreen use:

- apply liberally 15 minutes before sun exposure
- reapply at least every two hours
- use a water resistant sunscreen if swimming or sweating
- Sun Protection Measures. Spending time in the sun increases your risk of skin cancer and early skin aging. To decrease this risk, regularly use a sunscreen with a Broad Spectrum SPF value of 15 or higher and other sun protection measures including:
  - limit time in the sun, especially from 10 a.m. – 2 p.m.
  - wear long-sleeved shirts, pants, hats and sunglasses
- children under 6 months of age: ask a doctor

Inactive Ingredients

WATER\AQUA\EAU • BUTYLENE GLYCOL DICAPRYLATE/DICAPRATE • DIMETHICONE • METHYL TRIMETHICONE • DIPHENYLSILOXY PHENYL TRIMETHICONE • LAURYL PEG-9 POLYDIMETHYLSILOXYETHYL DIMETHICONE • GLYCERIN • BUTYLENE GLYCOL • PENTYLENE GLYCOL • PEG-10 DIMETHICONE • ALGAE (SEAWEED) EXTRACT • SESAMUM INDICUM (SESAME) SEED OIL • MEDICAGO SATIVA (ALFALFA) SEED POWDER • HELIANTHUS ANNUUS (SUNFLOWER) SEEDCAKE • PRUNUS AMYGDALUS DULCIS (SWEET ALMOND) SEED MEAL • EUCALYPTUS GLOBULUS (EUCALYPTUS) LEAF OIL • SODIUM GLUCONATE • COPPER GLUCONATE • CALCIUM GLUCONATE • MAGNESIUM GLUCONATE • ZINC GLUCONATE • TOCOPHERYL SUCCINATE • NIACIN • SESAMUM INDICUM (SESAME) SEED POWDER • CITRUS AURANTIFOLIA (LIME) PEEL EXTRACT • CODIUM TOMENTOSUM EXTRACT • ERYNGIUM MARITIMUM EXTRACT • LAMINARIA DIGITATA EXTRACT • SIGESBECKIA ORIENTALIS (ST. PAUL'S WORT) EXTRACT • ACETYL HEXAPEPTIDE-8 • MAGNESIUM SULFATE • ACRYLATES/STEARYL ACRYLATE/DIMETHICONE METHACRYLATE COPOLYMER • DIMETHICONE CROSSPOLYMER • DISTEARDIMONIUM HECTORITE • LAUROYL LYSINE • ETHYLHEXYLGLYCERIN • POLYHYDROXYSTEARIC ACID • YEAST EXTRACT\FAEX\EXTRAIT DE LEVURE • CAPRYLYL GLYCOL • LECITHIN • ISOPROPYL MYRISTATE • ISOSTEARIC ACID • ETHYLHEXYL PALMITATE • STEARIC ACID • POLYGLYCERYL-3 POLYRICINOLEATE • ALUMINA • ALUMINUM HYDROXIDE • TOCOPHEROL • TRIETHOXYCAPRYLYLSILANE • FRAGRANCE (PARFUM) • POTASSIUM SORBATE • ALCOHOL DENAT. • DISODIUM EDTA • BHT • LINALOOL • CITRONELLOL • GERANIOL • LIMONENE • HYDROXYCITRONELLAL • PHENOXYETHANOL • [+/- MICA • TITANIUM DIOXIDE (CI 77891) • IRON OXIDES (CI 77492) • IRON OXIDES (CI 77491) • IRON OXIDES (CI 77499)] <ILN44570>

Other information

- protect the product in this container from excessive heat and direct sun

PRINCIPAL DISPLAY PANEL - 12 g x 2 Container Carton

SKINCOLOR DE LA MER™

LA MER

the luminous lifting cushion foundation
broad spectrum SPF 20

total poids net wt. 0.84 oz./24g e (12g x 2)